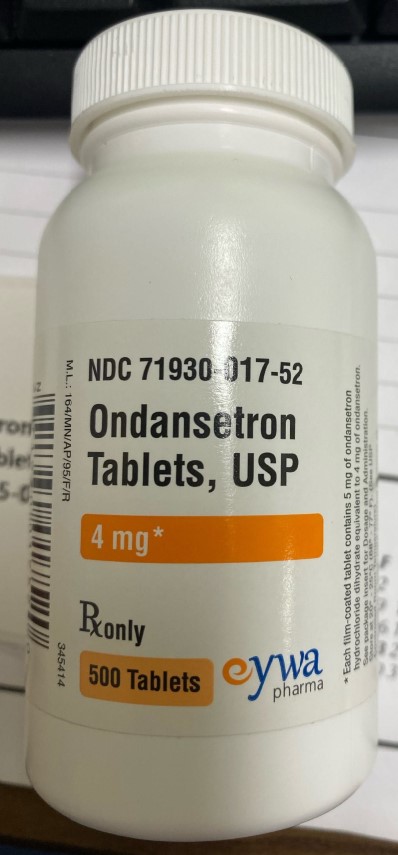 DRUG LABEL: Ondansetron
NDC: 80175-0017 | Form: TABLET
Manufacturer: Central Packaging
Category: prescription | Type: HUMAN PRESCRIPTION DRUG LABEL
Date: 20210224

ACTIVE INGREDIENTS: ONDANSETRON HYDROCHLORIDE 4 mg/1 1

DOSAGE FORMS AND STRENGTHS

Ondansetron Tablets USP, are available in the following strengths:4 mg – white, oval, film-coated tablets engraved with "4" on one side and “NO”on other side.8 mg – yellow, oval, film-coated tablets engraved with "8" on one side and "NO" on the other side.